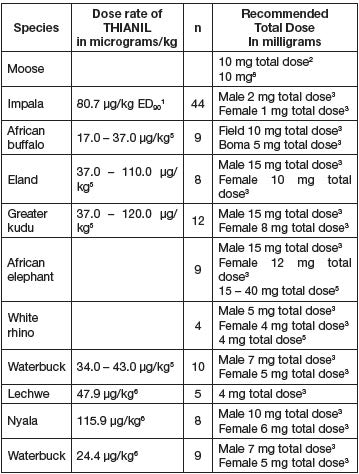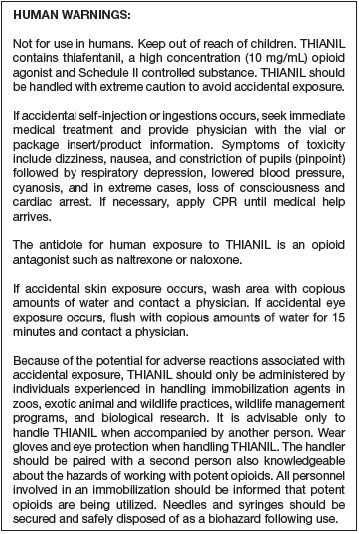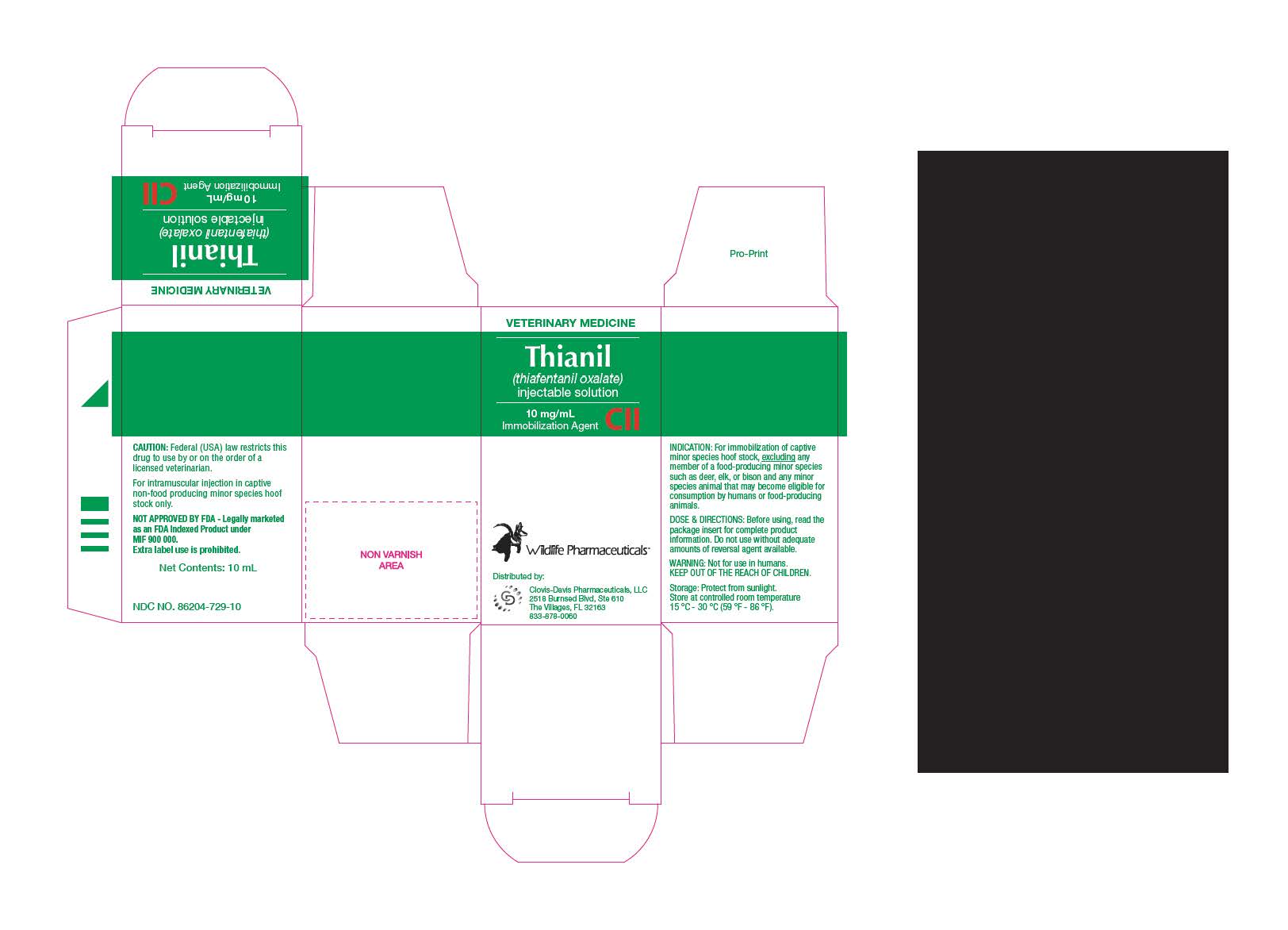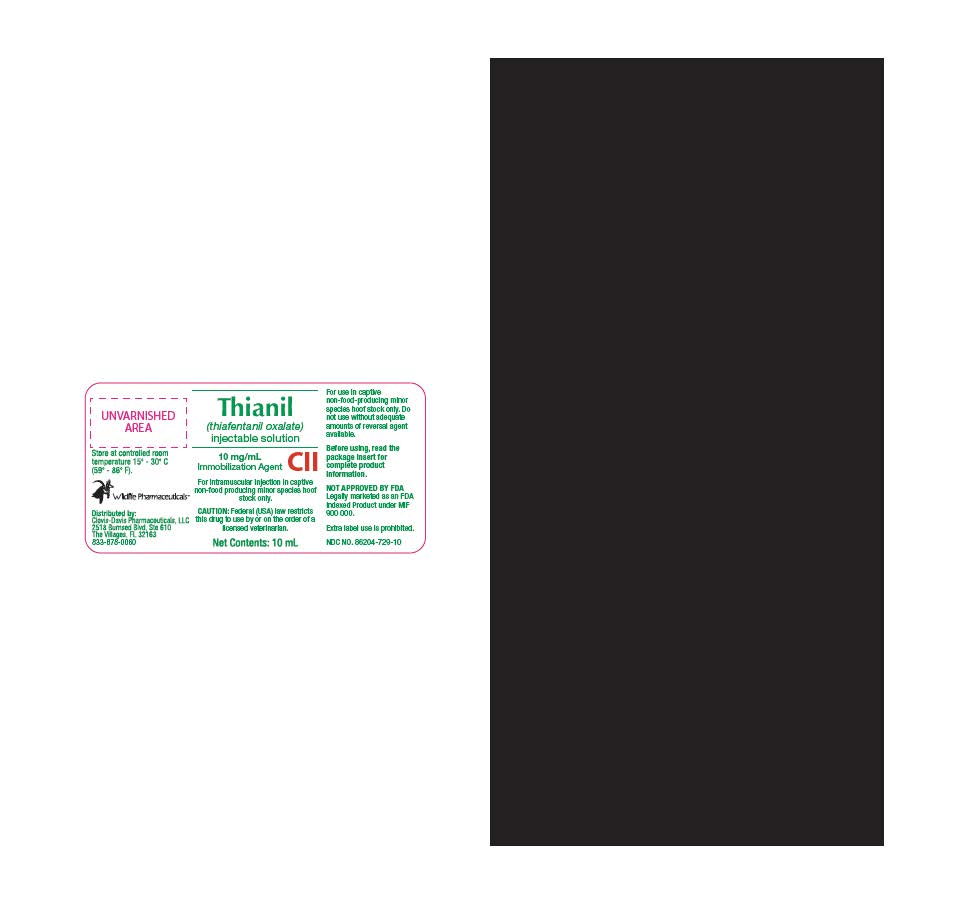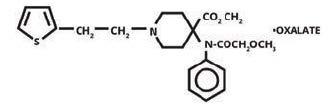 DRUG LABEL: Thianil
NDC: 86204-729 | Form: INJECTION, SOLUTION
Manufacturer: Clovis-Davis Pharmaceuticals LLC
Category: animal | Type: PRESCRIPTION ANIMAL DRUG LABEL
Date: 20251020
DEA Schedule: CII

ACTIVE INGREDIENTS: THIAFENTANIL OXALATE 10 mg/1 mL
INACTIVE INGREDIENTS: Methylparaben 1 mg/1 mL

THIANIL

PATIENT INFORMATION

Thianil
(thiafentanil oxalate)
Injectable solution
10 mg/mL

CII

For intramuscular injection in captive non-food-producing minor
species hoof stock only.

CAUTION: Federal (USA) law restricts this drug to use by or on the
order of a licensed veterinarian.

NOT APPROVED BY FDA Legally marked as an FDA Indexed
Product under MIF 900 000. Extra label use prohibited.

Note: In order to be legally marketed an animal drug product
intended for a minor species must be Approved, Conditionally
Approved, or Indexed by the FDA. THIS PRODUCT IS INDEXED.

Do not use this product without adequate amounts of reversal
agent available.

It is a violation of Federal Law to use this product in a manner other
than as directed in the labelling. The term minor species means
animals other than humans that are not major species. Major
species means cattle, horses, swine, chickens, turkeys, dogs,
and cats. As used on this label, a food-producing minor species
is considered to be a minor species of which some members
are bred, cultured, farmed, ranched, hunted, caught, trapped or
otherwise harvested for the purpose of having the animals or edible
products of the animals commercially distributed for consumption
by humans or food-producing animals in the United States.

DESCRIPTION:

Thiafentanil oxalate is 4-(Methoxycarbonyl)-4-
(N-phenylmethoxy-acetamido)-1-[2-(2-thienyl) ethyl] piperidinium
oxalate. Its molecular formula is C24H30N2O2S. Its molecular mass
is 506.57. Each mL of THIANIL contains 10 mg thiafentanil oxalate
and 0.1 % methylparaben.

Structural Formula:

PHARMACOLOGY:

Thiafentanil oxalate has a morphine-like
analgesic mode of action and produces rapid immobilization
following intramuscular injection.

INDICATION:

For immobilization of captive minor species hoof
stock, excluding any member of a food-producing minor species
such as deer, elk or bison and any minor species animal that may
become eligible for consumption by humans or food-producing
animals.
Use only when there is a reasonable certainty that the treated
animal will not be consumed by humans or food-producing
animals.

DOSAGE AND ADMINISTRATION:

Total doses used in captive minor species hoof stock to date have ranged from 1 mg (Impala)
to 15 mg (African elephant). Immobilization is usually achieved in
2 to 10 minutes following administration. The most effective dose
rate will vary due to the conditions of use.

The lower end of the dose range is suggested for those animals of quiet
temperament, under confinement, that have not been hotly pursued
prior to administration of the drug, or for animals in poor physical condition.
The upper end of the dose range is suggested for animals of
excitable temperament following extensive pursuit or in instances
where an extremely short chase time is desirable. The upper end of
the dose range may also be appropriate for animals being pursued
by vehicle or aircraft when an extremely quick immobilization time
is desired or when individuals are known to be highly excitable.
In all instances, all factors including nutritional, reproductive, and
health status of an animals as well as environmental conditions
(temperature, cover, and terrain) must be evaluated by the used
and the best professional judgement used.

DOSE CHART

The following doses are representative of doses used in field trials.

^1 Janssen, DL, GE Swan, JP Raath, SW McJames, JL Allen,
V de Vos, KE Williams, JM Anderson, and TH Stanley. 1993.
Immobilization and physiologic effects of narcotic A-3080 in
impala (Aepyceros melampus). J. Zoo Wildl. Med., 24: 11-18.
^2 Kreeger, TJ and JM Arnemo. 2007. Handbook of Wildlife Chemical
Immobilization, 3rd ed. For North and South American orders:
tkreeger@starband.net or Amazon.com.
^3 Lance, WR. 2008 Attachemtn C; Recommended Dosages
for Adult Animals South Africa and North America. Wildlife
Pharmaceuticals, Inc, fort Collins, CO 80524. P. 9-10.
^4 McJames, SW, IL Smith, TH Stanley, and G Painter. 1993. Elk
immobilization with potent opioids: A3080 vs. carfentanil. Proc.
Conf. Amer. Assoc. Zoo Vet., Saint Louis, Missouri. pp. 418-419.
^5 Raath, JP. 2005. Clinical Expert Report First Study. pp. 1-11.
^6 Raath, JP. 2005 Clinical Expert Report Second Study. pp. 11-22.
^7 Stanley, TH, SW McJames, J Kimball, JD Port, and NL Pace. 1988.
Immobilization of elk with A-3080. J. Wildl Mgmt. pp. 577-581.
^8 Stanley, TH, SW McJames, and J Kimball. 1989. Chemical
immobilization for the capture and transportation of big game.
Proc. Conf. Amer. Assoc. Zoo Vet. Greensboro, North Carolina.
pp. 13-14.

Inject dose deep into a large muscle mass of the neck, shoulder, back,
or hindquarter. Intra-thoracic, intra-abdominal, or subcutaneous
injection is to be avoided. To ensure proper dosage for animals
weighing less than 50 kg, remove the calculated dose of THIANIL
from the vial with a tuberculin syringe. Dilute appropriate volume with
sterile water for injection prior to administration. Operator should use
safe technique by working in pairs, wearing disposable latex gloves,
and wearing eye protection. Used syringes should be secured and
disposed of in an appropriate biohazard container.

ANTIDOTE:

TREXONILTM (naltrexone hydrochloride) is the recommended
antidote and rapidly reverses the effects of THIANIL.
Administer 10 mg TREXONILTM for each milligram of THIANIL.
The total calculated dose of TREXONILTM should be administered
intramuscular unless there is a medical or anesthetic emergency
requiring immediate reversal, then ¼ of the calculated dose should
be administered intravenously and ¾ of the calculated dose should
be administered intramuscularly. The entire dose can be safely
delivered intravenously but the operator should be prepared for
occasional extrapyramidal activity and signs, and/or very rapid
return to consciousness and mobility. Reversal of effects of THIANIL
are usually observed in 2 to 10 minutes, with differences resulting
from whether reversal is performed by intramuscular injection,
split between intravenous injection and intramuscular injection, or
completely delivered by intravenous injection.

CONTRAINDICATIONS:

THIANIL is not for use in minor species
hoof stock in the family Equidae. Do not use thiafentanil oxalate
in animals that display clinical signs of disease unless its use is
imperative to establish a diagnosis and/or administer therapeutic
agents. The effects of thiafentanil oxalate on reproductive
performance, pregnancy, and lactation have not been determined.
An opioid antagonist should always be drawn up, labelled, and
readily accessible prior to drawing up thiafentanil oxalate.

WARNINGS:

As with other opioids, all species immobilized with
THIANIL may show signs of excitement, tachycardia or bradycardia,
tachypnea or bradypnea, hypertension or hypotension, depressed
respiration, cyanosis, poikilothermia, and reaction to sudden noise.
Personnel should be advised of these potential opioid effects and
trained to respond appropriately.

PRECAUTIONS:

THIAFENTANIL OXALATE SHOULD NEVER BE
USED UNLESS AN ADEQUATE AMOUNT OF THE REVERSAL
AGENT, TREXONILTM (naltrexone hydrochloride), IS IMMEDIATELY
AVAILABLE. Veterinarians using THIANIL should be familiar with
clinical procedures such as measurement of pulse and respiration,
oxygen saturation, prevention of aspiration, relief of bloat, obstetrics,
control of shock and hemorrhage, recognition for hyperventilation,
heat exhaustion, capture myopathy, and the immobilization of
fractures, etc. In cases of severe excitement during induction or
delayed recovery, continued observation is necessary to correct any
of the above situations and to insure the animal does not injure itself.

STORAGE:

Store at controlled room temperature (59-86 °F) in
a facility consistent with appropriate Drug Enforcement Agency
regulations regarding Schedule II N (narcotic) Class drugs. Protect
from prolonged exposure to excessive heat.

HOW SUPPLIED:

THIANIL (thiafentanil oxalate) injectable solution
is supplied in a sterile 10 mL multiple use glass vial. Each mL of
THIANIL contains 10 mg thiafentanil and 0.1% methylparaben.

Wildlife PharmaceuticalsTM

Distributed by:
Clovis-Davis Pharmaceuticals, LLC
2518 Burnsed Blvd, Ste 610 The Villages, FL 32163
833-878-0060
NDC number: 86204-729-10

CARTON

VETERINARY MEDICINE

Thianil
(thiafentanil oxalate)
injectable solution

10mg/mL

Immobilization Agent

CII

Wildlife PharmaceuticalsTM

Distributed by:
Clovis-Davis Pharmaceuticals, LLC
2518 Burnsed Blvd, Ste 610 The Villages, FL 32163
833-878-0060

CAUTION: Federal (USA) law restricts this drug to use by or on the order of a licensed veterinarian.

For intramuscular injection in captive non-food producing minor species hoof stock only.

NOT APPROVED BY FDA - Legally marketed as an FDA Indexed Product under MIF 900 000.
Extra label use is prohibited.

Net Contents: 10mL

NDC NO. 86204-729-10

INDICATION: For immobilization of captive minor species hoof stock, excluding any member of a food-producing minor species such as deer, elk, or bison and any minor species animal that may become eligible for consumption by humans or food-producing animals.

DOSE & DIRECTIONS: Before using, read the package insert for complete product information. Do not use without adequate amounts of reversal agent available.

WARNING: Not for use in humans.
KEEP OUT OF THE REACH OF CHILDREN.

Storage: Protect from sunlight.
Store at controlled room temperature
15 °C - 30 °C (59 °F - 86 °F).

PACKAGE LABEL

VETERINARY MEDICINE

Thianil
(thiafentanil oxalate)
injectable solution

Store at controlled room temperature
15 °C - 30 °C (59 °F - 86 °F)

Wildlife PharmaceuticalsTM

Distributed by:

Clovis-Davis Pharmaceuticals, LLC
2518 Burnsed Blvd, Ste 610 The Villages, FL 32163
833-878-0060

10mg/mL

Immobilization Agent

CII

For intramuscular injection in captive non-food producing minor species hoof stock only.

CAUTION: Federal (USA) law restricts this drug to use by or on the order of a licensed veterinarian.

Net Contents: 10mL

For use in captive non-food -producing minor species hoof stock only.

Do not use without adequate amounts of reversal agent available.

Before using, read the package insert for complete product information.

NOT APPROVED BY FDA - Legally marketed as an FDA Indexed Product under MIF 900 000.
Extra label use is prohibited.

NDC NO. 86204-729-10